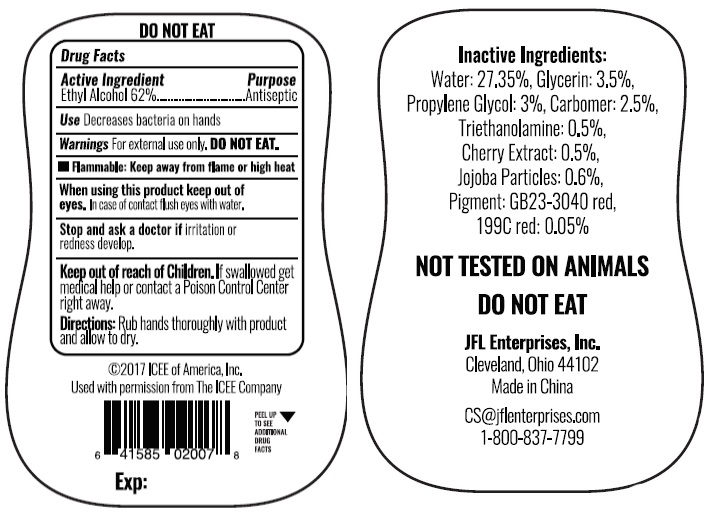 DRUG LABEL: Hand Sanitizer Cherry
NDC: 71246-4019 | Form: GEL
Manufacturer: JFL ENTERPRISES, INC
Category: otc | Type: HUMAN OTC DRUG LABEL
Date: 20180101

ACTIVE INGREDIENTS: ALCOHOL 62 mL/100 mL
INACTIVE INGREDIENTS: PROPYLENE GLYCOL; WATER; GLYCERIN; CARBOMER HOMOPOLYMER TYPE B (ALLYL SUCROSE CROSSLINKED); TRIETHANOLAMINE 2-CYCLOHEXYL-4,6-DINITROPHENOLATE; JOJOBA ACID; PIGMENT RED 1; CHERRY

ANTIBACTERIAL HAND GEL ICEE Cherry

Active ingredient

Alcohol 62%

Purpose

Antiseptic Hand Sanitizer

Use

Decrease bacteria on hands

Warnings

External Use Only. DO NOT EAT.

Keep out of reach of children

if swallowed get medical help or contact a Poison Control Center right away.

WARNINGS

Flammable: Keep away from flame or high heat

Directions

Rub hands thoroughly with product and allow to dry.

Inactive Ingredient

Carbomer, Glycerin, Jojoba Particles, Cherry Extract, Pigment Red GB23-3020, RED 199C, Propylene Glycol, Triethanolamine, Water

Stop and Ask a doctor if

Irritation or redness develop.